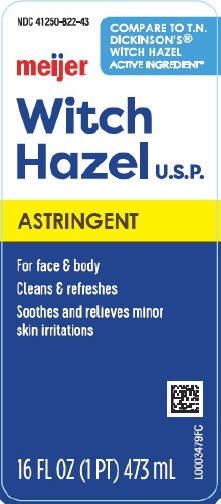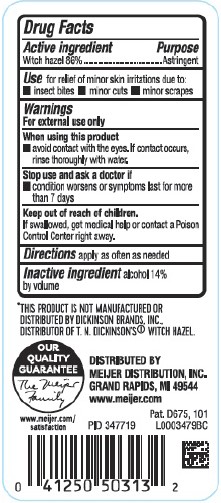 DRUG LABEL: Witch Hazel
NDC: 41250-822 | Form: LIQUID
Manufacturer: Meijer, Inc.
Category: otc | Type: HUMAN OTC DRUG LABEL
Date: 20260219

ACTIVE INGREDIENTS: WITCH HAZEL 86 kg/100 L
INACTIVE INGREDIENTS: ALCOHOL

Meijer 822.001/822AA
Witch Hazel

Active ingredient

Witch hazel 86%

Purpose

Astringent

Use

for relief of minor skin irritations due to:

- insect bites
- minor cuts
- minor scrapes

Warnings

For external use only

When using this product

- avoid contact with the eyes. If contact occurs, rinse thoroughly with water.

Stop use and ask a doctor if

- condition worsens or symptoms persist for more than 7 days

Keep out of reach of children.

If swallowed, get medical help or contact a Poison Control Center right away.

Directions

apply as often as needed

Inactive ingredient

alcohol 14% by volume

Disclaimer

*THIS PRODUCT IS NOT MANUFACTURED OR DISTRIBUTED BY DICKINSON BRANDS, INC., DISTRIBUTOR OF T.N. DICKINSON'S® WITCH HAZEL.

Adverse Reaction

OUR QUALITY GUARANTEE

The Meijer Family

www.meijer.com/satisfaction

DISTRIBUTED BY MEIJER DISTRIBUTION, INC.

GRAND RAPIDS, MI 49544

www.meijer.com

PID 347719

Pat. D675, 101

principal display panel

NDC 41250-822-43

COMPARE TO T.N. DICKINSON'S®WITCH HAZEL ACTIVE INGREDIENT*

meijer®

Witch Hazel U.S.P.

Astringent

For Face & Body

Cleans & Refreshes

Soothes and relieves minor skin irritations

16 FL OZ (1 PT) 473 mL